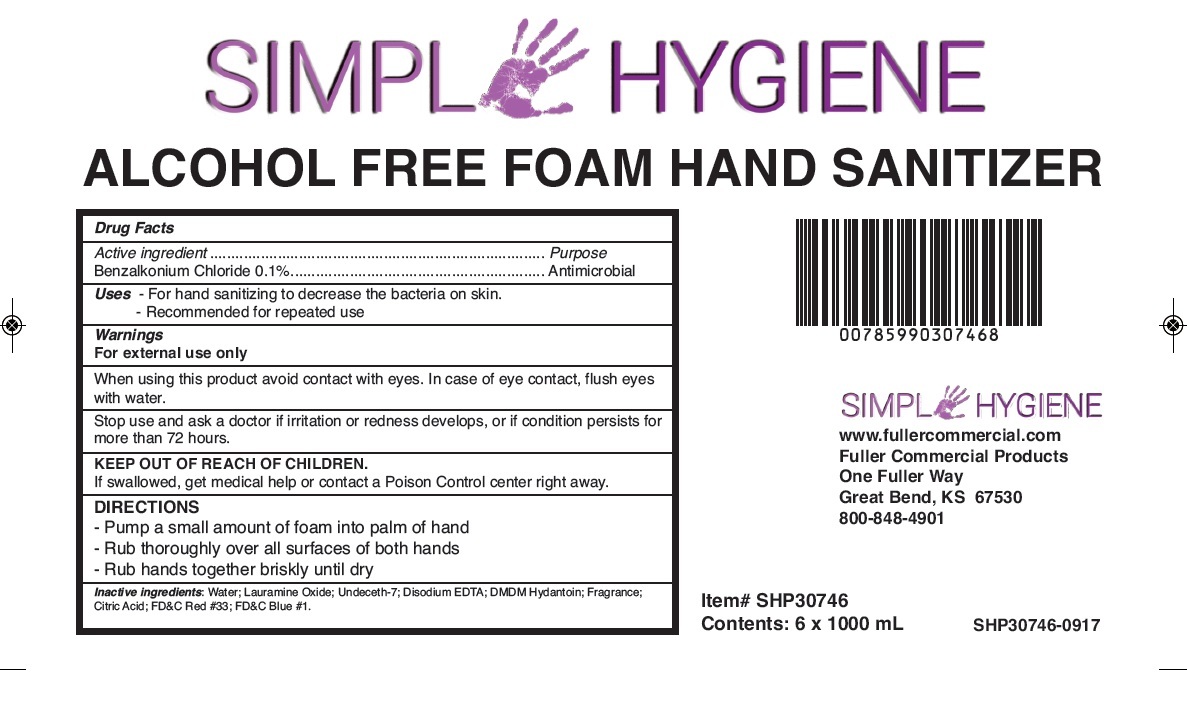 DRUG LABEL: Alcohol Free Hand Sanitizer
NDC: 60933-200 | Form: AEROSOL, FOAM
Manufacturer: FULLER INDUSTRIES, INC
Category: otc | Type: HUMAN OTC DRUG LABEL
Date: 20231028

ACTIVE INGREDIENTS: BENZALKONIUM CHLORIDE 1 mg/1 mL
INACTIVE INGREDIENTS: WATER; LAURAMINE OXIDE; UNDECETH-7; EDETATE DISODIUM ANHYDROUS; DMDM HYDANTOIN; CITRIC ACID MONOHYDRATE; D&C RED NO. 33; FD&C BLUE NO. 1

Alcohol Free Foam Hand Sanitizer

Active ingredient

Benzalkonoium Chloride 0.1%

Purpose

Antimicrobial

Uses

- For hand sanitizing to decrease the bacteria on skin.

- Recommended for repeated use

Warnings

For external use only

When using this product

avoid contact with eyes In case of eye contact, flush eyes with water.

Stop use and ask a doctor

if irritation or redness develops, or if condition persists for more than 72 hours

KEEP OUT OF REACH OF CHILDREN

If swallowed, get medical help or contact a Poison Control center right away.

DIRECTIONS

- Pump a small amount of foam into palm of hand

- Rub thoroughly over all surfaces of both hands

- Rub hands together briskly until dry

Inactive Ingredients:

Water; Lauramine Oxide; Undeceth-7; Disodium EDTA; DMDM Hydantoin; Fragrance; Citric Acid; FD&C Red #33; FD&C Blue #1/